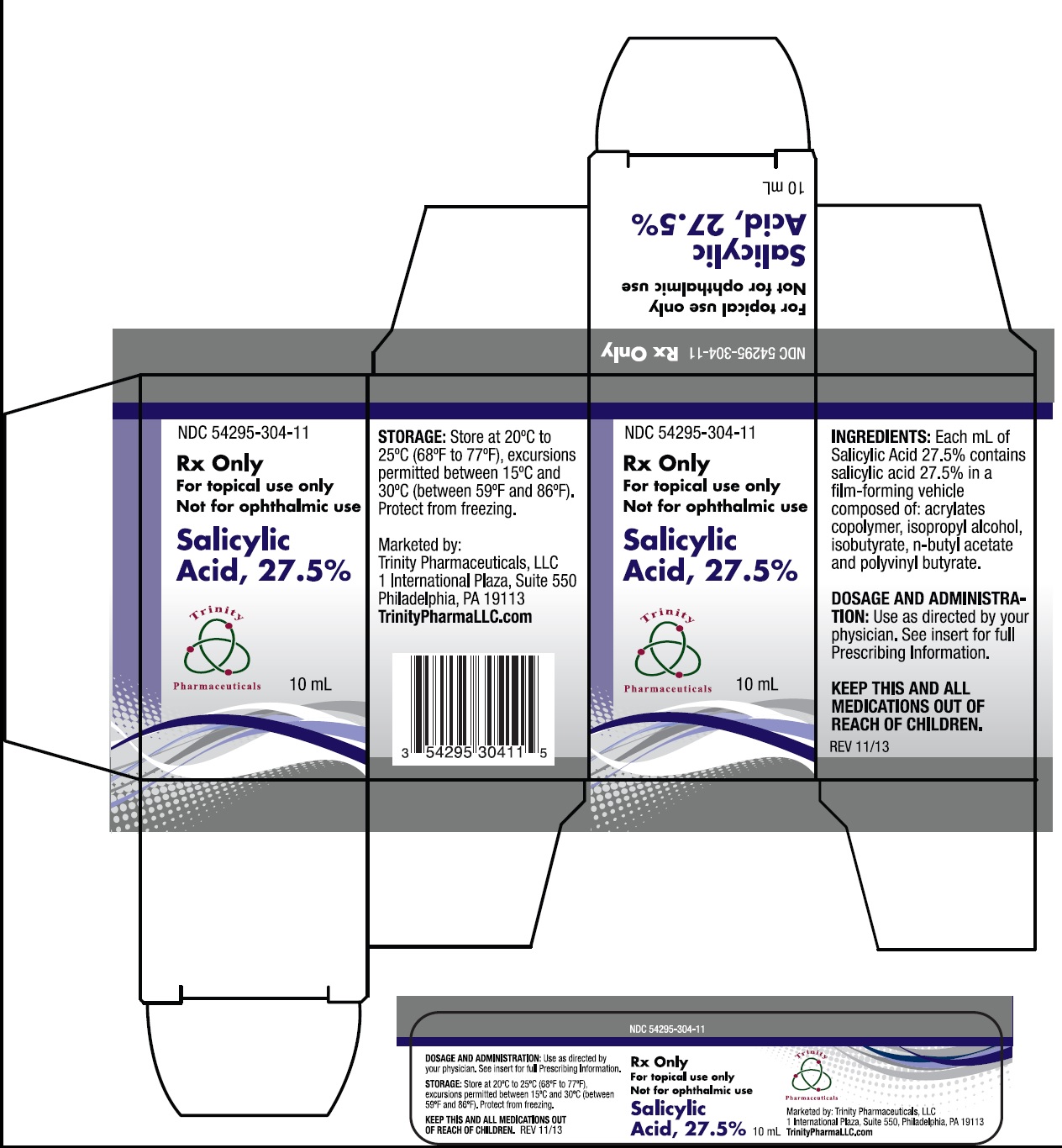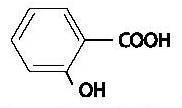 DRUG LABEL: Salicylic Acid
NDC: 54295-304 | Form: SOLUTION
Manufacturer: Trinity Pharmaceuticals, LLC
Category: prescription | Type: HUMAN PRESCRIPTION DRUG LABEL
Date: 20230322

ACTIVE INGREDIENTS: SALICYLIC ACID 275 mg/1 mL
INACTIVE INGREDIENTS: ISOPROPYL ALCOHOL; BUTYL ACETATE

Salicylic Acid, 27.5%

PATIENT INFORMATION

Rx only

FOR DERMATOLOGICAL USE ONLY. NOT FOR OPHTHALMIC, ORAL OR INTRAVAGINAL USE.

DESCRIPTION

Salicylic Acid, 27.5% is a topical preparation containing 27.5% Salicylic Acid in a film-forming vehicle composed of: acrylates copolymer, isopropyl alcohol, isobutyrate, n-butyl acetate, and polyvinyl butyrate. The pharmacologic activity of this medication is generally attributed to the keratolytic activity of salicylic acid which is incorporated into a film-forming vehicle designed to cover the wart without the need for a bandage. The chemical structural formula of salicylic acid is:

CLINICAL PHARMACOLOGY

Although the exact mode of action for salicylic acid in the treatment of warts is unknown, its activity appears to be associated with its keratolytic action, which results in mechanical removal of epidermal cells infected with wart viruses.

INDICATIONS AND USES

Salicylic Acid, 27.5% is indicated for the topical treatment and removal of common warts and plantar warts.

CONTRAINDICATIONS

Salicylic Acid, 27.5% should not be used by diabetics or patients with impaired blood circulation. Salicylic Acid, 27.5% should not be used on moles, birthmarks, unusual warts with hair growing from them or warts on the face.

PRECAUTIONS

Salicylic Acid, 27.5% is for external use only. Do not permit Salicylic Acid, 27.5% to contact eyes or mucous membranes. If contact with eyes or mucous membranes occurs, immediately flush with water for 15 minutes. Salicylic Acid, 27.5% should not be allowed to contact normal skin surrounding the wart. Treatment should be discontinued if excessive irritation occurs. Salicylic Acid, 27.5% is flammable and should be kept away from fire or flame. Keep bottle tightly capped when not in use.

ADVERSE REACTIONS

A localized irritant reaction may occur if Salicylic Acid, 27.5% is applied to the normal skin surrounding the wart. Any irritation may normally be controlled by temporarily discontinuing use and by applying the medication only to the wart site when treatment is resumed.

DOSAGE AND ADMINISTRATION

Prior to application of Salicylic Acid, 27.5% soak wart in warm water for five minutes. Remove any loosened tissue by gently rubbing with a brush, wash cloth, emery board or pumice stone. Dry thoroughly. Using the brush applicator supplied, apply twice to entire wart surface, allowing the first application to dry before applying the second. Treatment should be once or twice a day and should continue as directed by physician. Be careful not to apply to surrounding skin. Clinically visible improvement will normally occur during the first or second week of therapy. Maximum resolution may be expected after four to six weeks of drug use.

HOW SUPPLIED

Salicylic Acid, 27.5% is supplied in 10 mL amber glass bottles with brush applicator - NDC 54295-304-11.

Store at 20ºC to 25ºC (68ºF to 77ºF)., excursions permitted between 15ºC and 30ºC (between 59ºF and 86ºF). Brief exposure to temperatures up to 40ºC (104ºF) may be tolerated provided the mean kinetic temperature does not exceed 25ºC (77ºF); however, such exposure should be minimized. Protect from freezing.

KEEP THIS AND ALL MEDICATIONS OUT OF REACH OF CHILDREN.

Marketed By:
Trinity Pharmaceuticals LLC
1 International Plaza, Suite 550
Philadelphia, PA 19113
TrinityPharmaLLC.com
REV 11/13

Salicylic Acid, 27.5% 10 mL Container Label Principal Display Panel Text:

NDC 54295-304-11

Rx only

For topical use only
Not for ophthalmic use

Salicylic Acid, 27.5%
10 mL